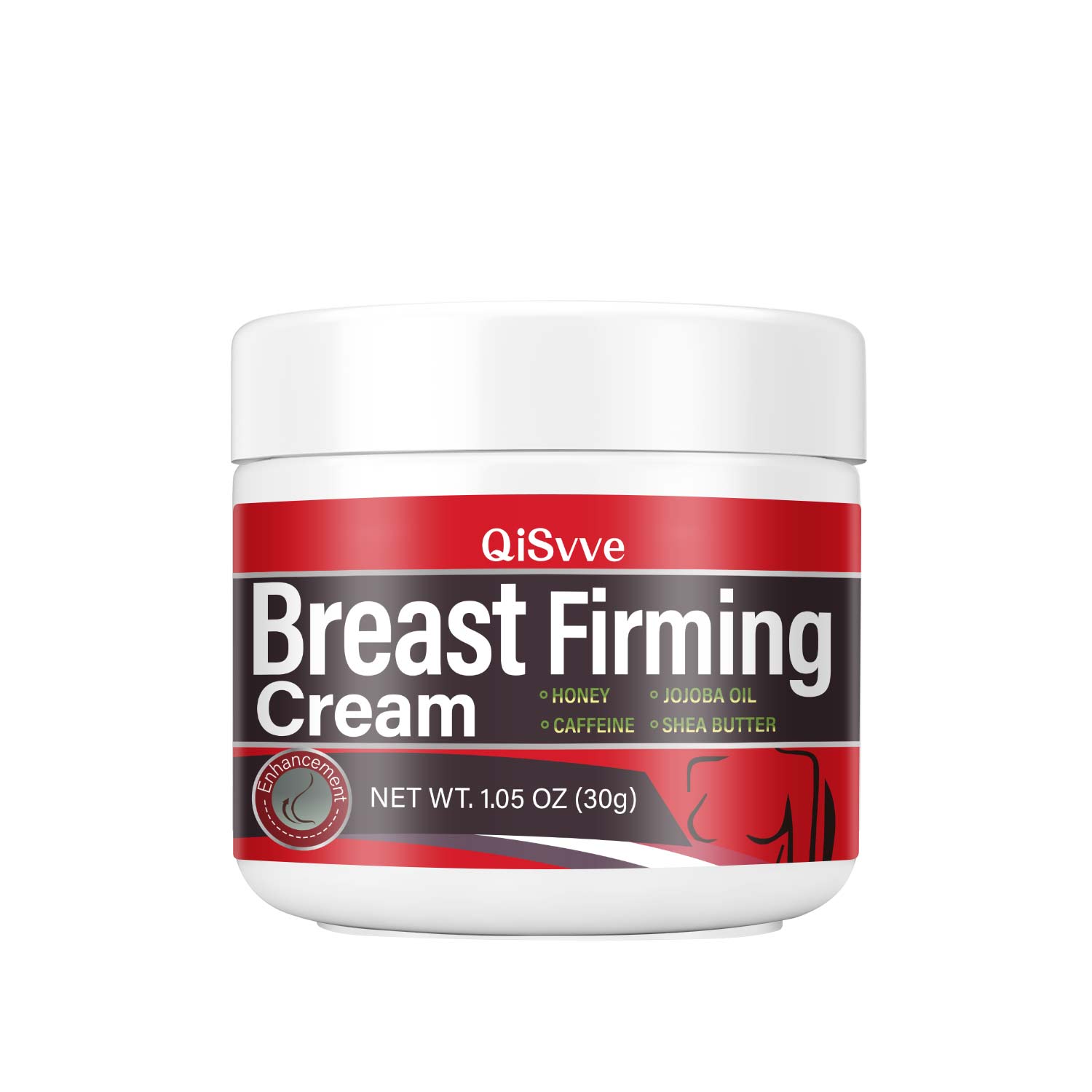 DRUG LABEL: Breast Firming Cream
NDC: 84117-024 | Form: CREAM
Manufacturer: Shenzhen Hengkaifeng Commerce and Trade Co., Ltd
Category: otc | Type: HUMAN OTC DRUG LABEL
Date: 20240905

ACTIVE INGREDIENTS: SUCROSE STEARATE 0.1 g/100 g
INACTIVE INGREDIENTS: WATER; CAFFEINE; HONEY; JOJOBA OIL; SHEA BUTTER; XANTHAN GUM

ACTIVE INGREDIENT

Sucrose Stearate

Purpose

Nourish skin

Use

Apply appropriate amount of product to skin

Warnings

For external use only,

Do not use this if you have very sensitive skin or if you are sensitive to benzoyl peroxide.

When using this product

keep away from eyes, lips and mouth

wavoid unnecessary sun exposure and use a sunscreen
avoid contact with hair or dyed fabric, including carpet and clothing which may be bleached by this product
skin irritation may occur, characterized by redness, burning, itching, peeling, or possibly
swelling. Mild irritation may be reduced by using the product less frequenty or in a lower concentration.
Ifirritation becomes severe,discontinue use; ifirritation still continues, consulta doctor
wusing other topical acne medication at the same time or immediately following the use of this product may
increase dryness or iritation of the skin, lf this occurs, only one medication should be used unless directed
by a doctor.

Keep out of reach of children.tfswallowed, get help or contact
a Poison Control Center right away.Avoid contact with the eyes. lf contact occurs,flush thoroughly with water.

Directions Of Safe Use:

Cleanse skin thoroughly before appying. Cover the enire afected
area with a thin layer 1-3 times daiy. lf bothersome dryness or peeing occurs, reduce application to once a day.

Other information

Keep tightly closed.Avoid storing at extreme temperatures (below 40° fand above 100° F).

Inactive ingredients

Water
Macadamia Ternifolia Seed Oil
Momordica Charantia Fruit Extract
Caffeine
Vitamin E
Honey
Jojoba oil
Shea Butter
Xanthan Gum
Rosa Rugosa Flower Oil
Sodium Hyaluronate

DOSAGE AND ADMINISTRATION

● adults and children 12 years of age and older:
● apply at least a 1-inch strip of the product onto a soft bristle toothbrush.
● brush teeth thoroughly for at least 1 minute twice a day (morning and evening),
and not more than 3 times a day, or as recommended by a dentist or doctor.
Make sure to brush all sensitive areas of the teeth. Minimize swallowing. Spit out
after brushing.
● children under 12 years of age: Consult a dentist or doctor.